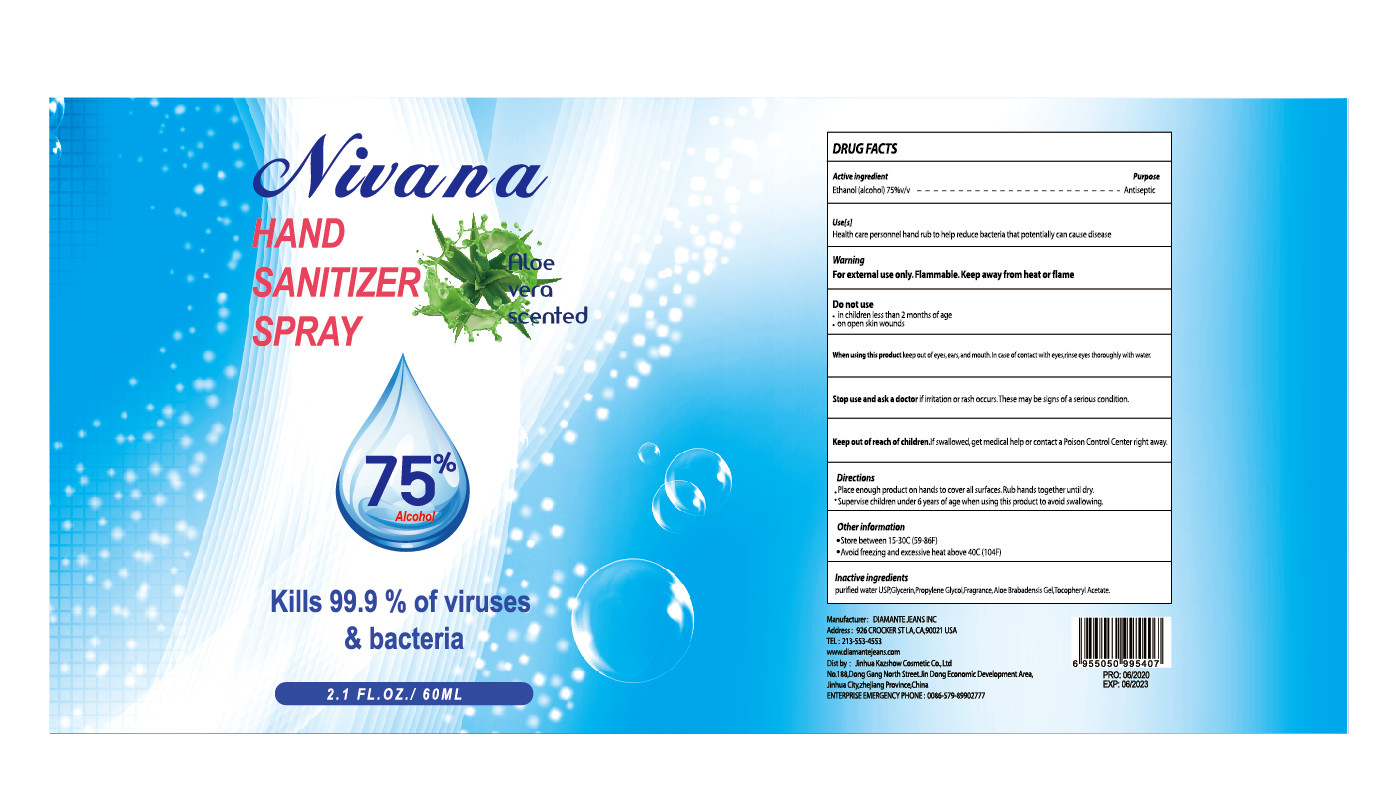 DRUG LABEL: Nivana  HAND SANITIZER
NDC: 54248-007 | Form: SPRAY
Manufacturer: JINHUA KAZSHOW COSMETICS CO., LTD.
Category: otc | Type: HUMAN OTC DRUG LABEL
Date: 20200611

ACTIVE INGREDIENTS: ALCOHOL 45 mL/60 mL
INACTIVE INGREDIENTS: WATER; PROPYLENE GLYCOL; FRAGRANCE LAVENDER & CHIA F-153480; ALOE; .ALPHA.-TOCOPHEROL; GLYCERIN

DOSAGE AND ADMINISTRATION

●Store between 15-30°C(59-86°F)
●avoid feezing and excessive heat above 40°C(104°F)

INACTIVE INGREDIENT

Purified water USP, Glycerin, Propylene Glycol, Fragrance，Aloe Barbadensis (Aloe Vera) Gel, Tocopheryl Acetate (Vitamin E)

INDICATIONS AND USAGE

Place enough productonhands tocover alsurfaces.Ruibhands togetherunti diry.

ACTIVE INGREDIENT

Alcohol

keep out of reach of children

PURPOSE

Disinfection
Sterilization

WARNINGS

For external use only. Flammable. Keep away from heat or flame